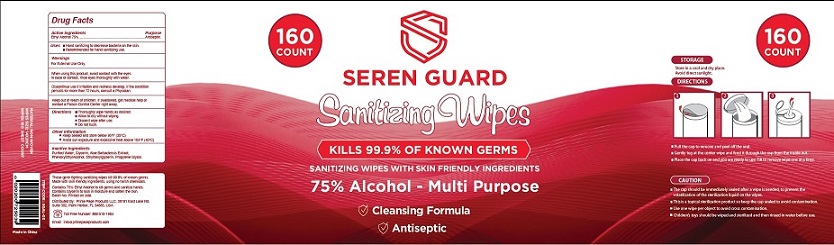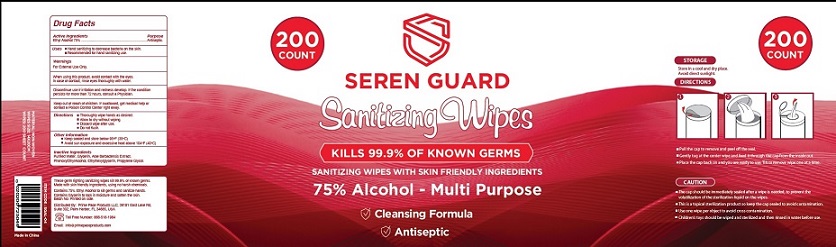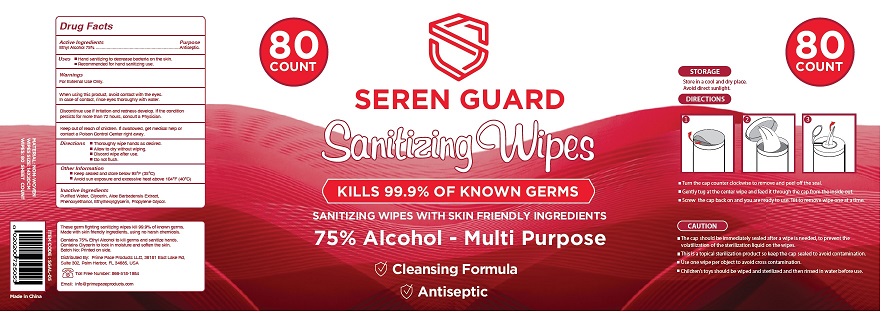 DRUG LABEL: SEREN GUARD Sanitizing Wipes
NDC: 79183-301 | Form: PATCH
Manufacturer: Prime Pace Products LLC
Category: otc | Type: HUMAN OTC DRUG LABEL
Date: 20201206

ACTIVE INGREDIENTS: ALCOHOL 4.9 g/1 1
INACTIVE INGREDIENTS: WATER; GLYCERIN; ALOE VERA FLOWER; PHENOXYETHANOL; ETHYLHEXYLGLYCERIN; PROPYLENE GLYCOL

SEREN GUARD Sanitizing Wipes

Drug Facts

Active Ingredient(s)

Ethyl Alcohol 75%

Purpose

Antiseptic

Uses

■ Hand sanitizing to decrease bacteria on the skin.
■ Recommended for hand sanitizing use.

Warnings

For external use only.

When using this product, avoid contact with the eyes.
In case of contact, rinse eyes thoroughly with water.

STOP USE

Discontinue use if irritation and redness develop. If the condition
persists for more than 72 hours, consult a Physician.

Keep out of reach of children. If swallowed, get medical help or contact a Poison Control Center right away.

Directions

■ Thoroughly wipe hands as desired.
■ Allow to dry without wiping.
■ Discard wipe after use.
■ Do not flush.

Other Information

■ Keep sealed and store below 95°F (35°C)
■ For External Use Only. Avoid sun exposure and excessive heat above 104°F (40°C)

Inactive Ingredients

Purified Water, Glycerin, Aloe Barbadensis Extract,
Phenoxyethanol, Ethylhexylglycerin, Propylene Glycol.

Package Label - Principal Display Panel

80
COUNT

SEREN GUARD

Sanitizig Wipes

KILLS 99.9% OF KNOWN GERMS

SANITIZING WIPES WITH SKIN FRIENDLY INGREDIENTS

75% Alcohol - Multi Purpose

Cleansing Formula

These germ fighting sanitizing wipes kill 99.9% of known germs.
Made with skin friendly ingredients, using no harsh chemicals.

Contains 75% Ethyl Alcohol to kill germs and sanitize hands.
Contains Glycerin to lock in moisture and soften the skin.
Batch No: Printed on bag.

These germ fighting sanitizing wipes kill 99.9% of known germs.
Made with skin friendly ingredients, using no harsh chemicals.
Contains 75% Ethyl Alcohol to kill germs and sanitize hands.
Contains Glycerin to lock in moisture and soften the skin.

Batch No: Printed on side.

Distributed By: Prime Pace Products LLC, 36181 East Lake Rd,
Suite 302, Palm Harbor, FL 34685, USA

Toll Free Number: 866-518-1984
Email: info@primepaceproducts.com

ITEM CODE: SGAL-01
0 0 0 0 2 0 2 0 0 6 0 6 0

Made in China

MATERIAL: NON-WOVEN
WIPES SIZE: 14X20CM
WIPES: 200 SHEET COUNT

80 Count

160 Count

200 Count

res